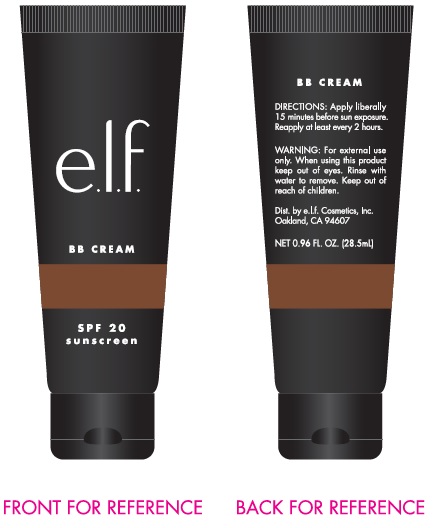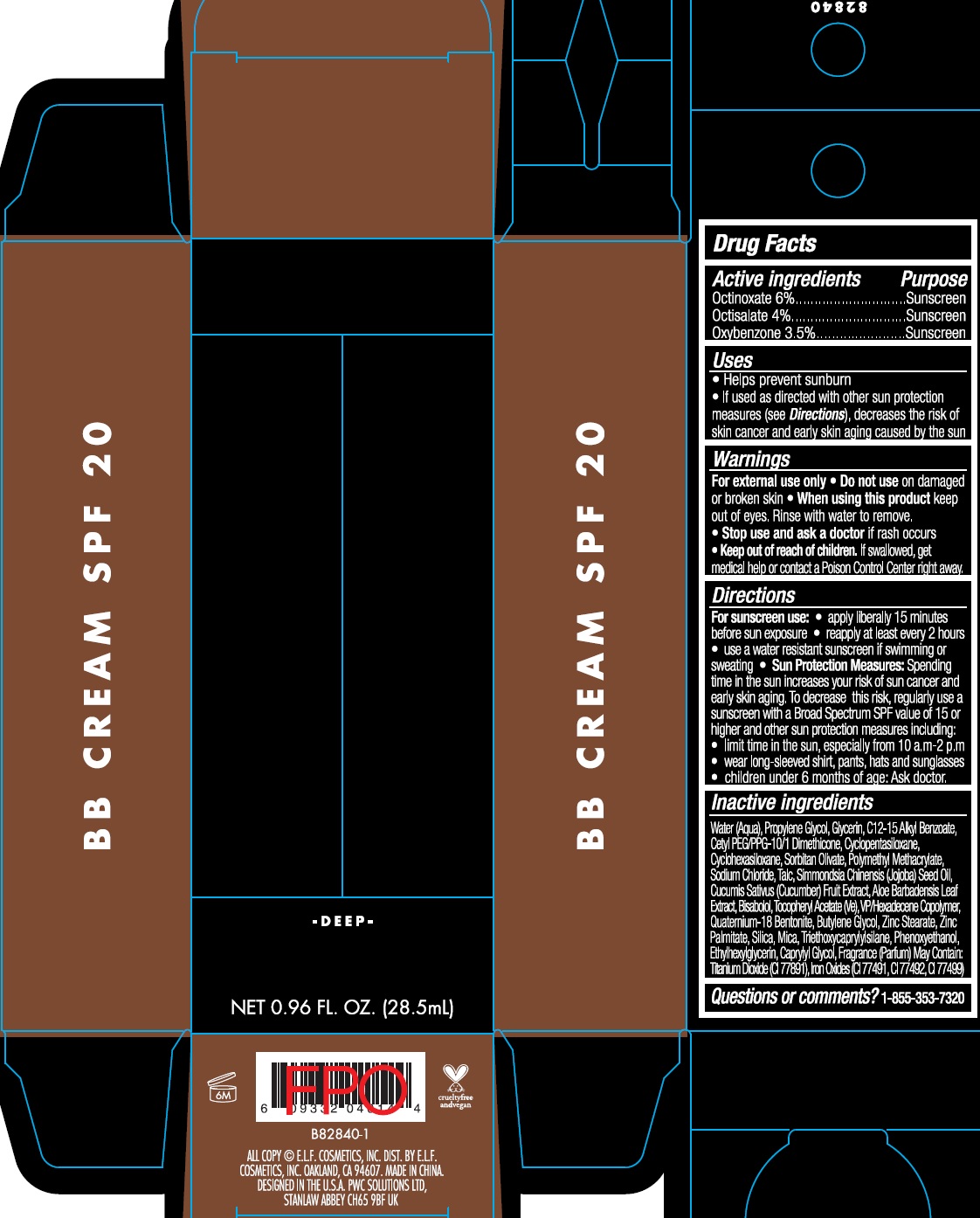 DRUG LABEL: BB SPF20
NDC: 76354-450 | Form: CREAM
Manufacturer: e.l.f. Cosmetics, Inc
Category: otc | Type: HUMAN OTC DRUG LABEL
Date: 20241212

ACTIVE INGREDIENTS: OCTINOXATE 60 mg/1 mL; OCTISALATE 40 mg/1 mL; OXYBENZONE 35 mg/1 mL
INACTIVE INGREDIENTS: WATER; PROPYLENE GLYCOL; GLYCERIN; CYCLOMETHICONE 5; ALKYL (C12-15) BENZOATE; CYCLOMETHICONE 6; SORBITAN OLIVATE; POLY(METHYL METHACRYLATE; 450000 MW); SODIUM CHLORIDE; TALC; JOJOBA OIL; CUCUMBER; ALOE VERA LEAF; LEVOMENOL; .ALPHA.-TOCOPHEROL ACETATE; VINYLPYRROLIDONE/HEXADECENE COPOLYMER; BENTOQUATAM; BUTYLENE GLYCOL; ZINC STEARATE; ZINC PALMITATE; SILICON DIOXIDE; MICA; TRIETHOXYCAPRYLYLSILANE; PHENOXYETHANOL; ETHYLHEXYLGLYCERIN; CAPRYLYL GLYCOL

BB Cream SPF20

Active ingredients

Octinoxate 6%

Octisalate 4%

Oxybenzone 3.5%

Purpose

Sunscreen

Uses

- Helps prevent sunburn
- If used as directed with other sun protection measures (see Directions), decreases the risk of skin cancer and early skin aging caused by the sun

Warnings

For external use only

Do not use

- on damaged or broken skin

When using this product

- keep out of eyes. Rinse with water to remove.

Stop use and ask a doctor

if rash occurs

Keep out of reach of children.

If swallowed, get medical help or contact a Poison Control Center right away.

Directions

- For sunscreen use:
- apply liberally 15 minutes before sun exposure
- reapply at least every 2 hours
- use a water resistant sunscreen if swimming or sweating
- Spending time in the sun increases your risk of sun cancer and early skin aging. To decrease this risk, regularly use a sunscreen with a Broad Spectrum SPF value of 15 or higher and other sun protection measures including: Sun Protection Measures:
- limit time in the sun, especially from 10 a.m.-2 p.m
- wear long-sleeved shirts, pants, hats and sunglasses
- children under 6 months of age: Ask doctor.

Inactive ingredients

Water (Aqua), Propylene Glycol, Glycerin, C12-15 Alkyl Benzoate, Cetyl PEG/PPG-10/1 Dimethicone, Cyclopentasiloxane, Cyclohexasiloxane, Sorbitan Olivate, Polymethyl Methacrylate, Sodium Chloride, Talc, Simmondsia Chinensis (Jojoba) Seed Oil, Cucumis Sativus (Cucumber) Fruit Extract, Aloe Barbadensis Leaf Extract, Bisabolol, Tocopheryl Acetate (Ve), VP/Hexadecene Copolymer, Quaternium-18 Bentonite, Butylene Glycol, Zinc Stearate, Zinc Palmitate, Silica, Mica, Triethoxycaprylylsilane, Phenoxyethanol, Ethylhexylglycerin, Caprylyl Glycol, Fragrance (Parfum) May Contain: Titanium Dioxide (CI 77891), Iron Oxides (CI 77491, CI 77492, CI 77499)

Questions or comments?

1-855-353-7320